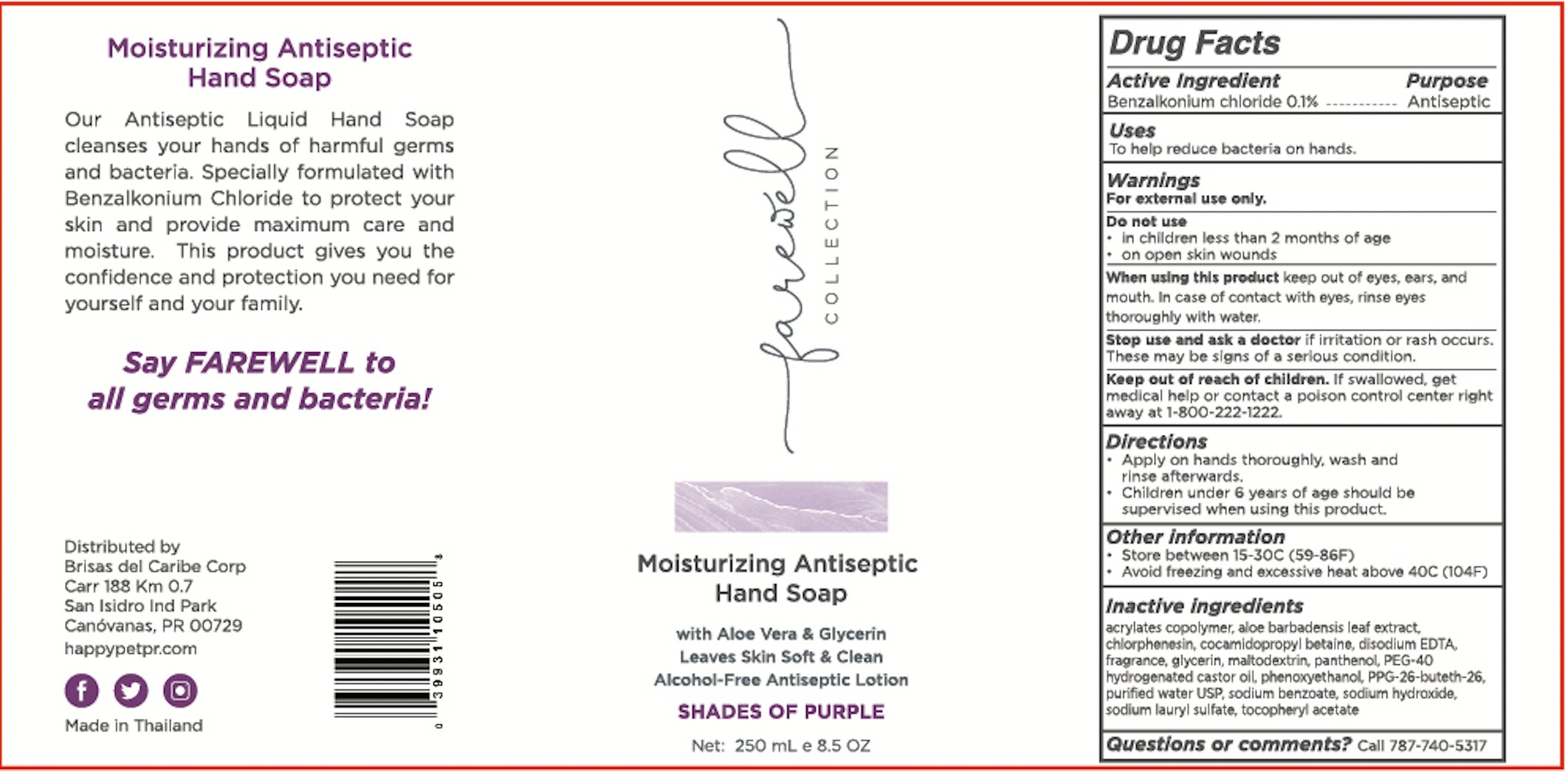 DRUG LABEL: Farewell Collection
NDC: 12961-116 | Form: SOAP
Manufacturer: Brisas del Caribe Corp.	
Category: otc | Type: HUMAN OTC DRUG LABEL
Date: 20221214

ACTIVE INGREDIENTS: BENZALKONIUM CHLORIDE 0.1 mg/100 mL
INACTIVE INGREDIENTS: CHLORPHENESIN; .ALPHA.-TOCOPHEROL ACETATE; EDETATE DISODIUM ANHYDROUS; PANTHENOL; MALTODEXTRIN; POLYOXYL 40 HYDROGENATED CASTOR OIL; ACRYLATES CROSSPOLYMER-6; SODIUM BENZOATE; ALOE VERA LEAF; PPG-26-BUTETH-26; GLYCERIN; WATER; COCAMIDOPROPYL BETAINE; PHENOXYETHANOL; FD&C YELLOW NO. 5; FD&C BLUE NO. 1; SODIUM LAURYL SULFATE; SODIUM HYDROXIDE

Brisas-Paveemol Hand Soap Purple

Active Ingredient(s)

Benzalkonium chloride 0.1%

Purpose

Antiseptic

Use

To help reduce bacteria on hands.

Warnings

For external use only.

Do not use

- in children less than 2 months of age
- on open skin wounds

When using this product keep out of eyes, ears, and mouth. In case of contact with eyes, rinse eyes thoroughly with water.
Stop use and ask a doctor if irritation or rash occurs. These may be signs of a serious condition.
Keep out of reach of children. If swallowed, get medical help or contact a Poison Control Center right away.

Stop use and ask a doctor if irritation or rash occurs. These may be signs of a serious condition.

Keep out of reach of children. If swallowed, get medical help or contact a Poison Control Center right away 1 800-222-1222

Directions

Apply on hands thoroughly, wash and rinse afterward.

Children under 6 years of age should be supervised when using this product.

Other information

- Store in between 15-30C (59-86F)
- Avoid freezing and excessive heat above 40C (104F)

Inactive ingredients

acrylates copolymer, aloe barbadensis leaf extract, chlorphenesin, cocamidopropyl betaine, disodium EDTA, glycerin, maltodextrin, panthenol, PEG-40 hydrogenated castor oil, phenoxyethanol, PPG-26-Buteth-26, purified water USP, sodium benzoate, sodium hydroxide, sodium lauryl sulfate, tocopheryl acetate

Package Label - Principal Display Panel

250 mL NDC:12961-116-11